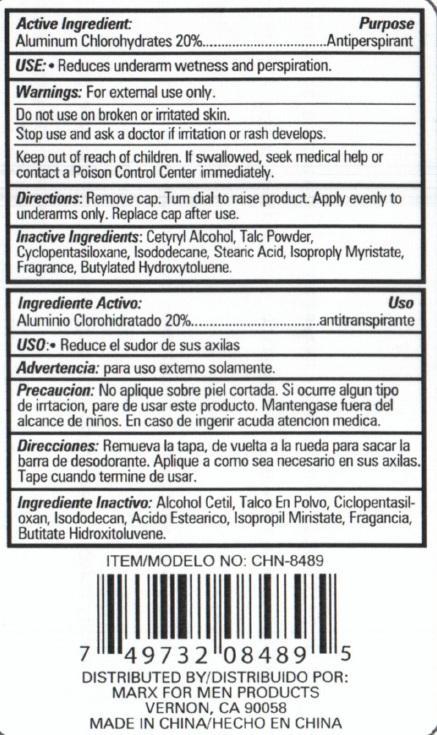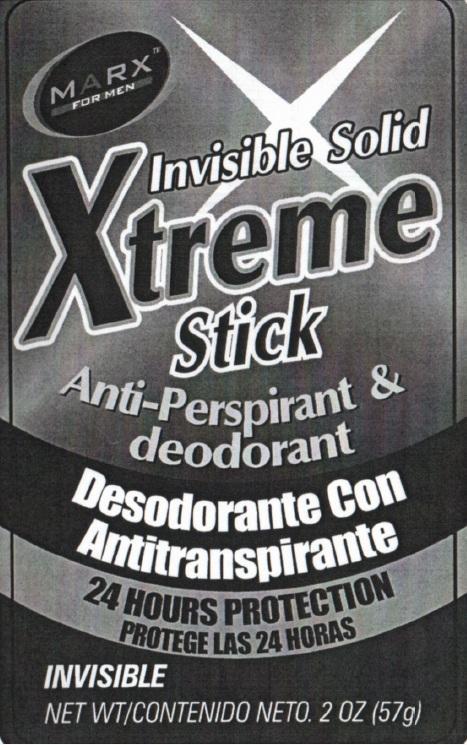 DRUG LABEL: Xtreme Stick Anti-Perspirant and Deodorant
NDC: 50523-489 | Form: CREAM
Manufacturer: VOLUME DISTRIBUTORS
Category: otc | Type: HUMAN OTC DRUG LABEL
Date: 20140804

ACTIVE INGREDIENTS: ALUMINUM CHLOROHYDRATE 20 g/100 g
INACTIVE INGREDIENTS: TALC; CYCLOMETHICONE 5; ISODODECANE; STEARIC ACID; ISOPROPYL MYRISTATE; BUTYLATED HYDROXYTOLUENE

MARKS FOR MEN XTREME STICK INVISIBLE SOLID ANTI-PERSPIRANT AND DEODORANT

Active Ingredient:

Aluminum Chlorohydrate 20%

PURPOSE

Antiperspirant

INDICATIONS AND USAGE

Use: Reduces underarm wetness and perspiration.

Warnings: for external use only.

Do not use on broken or irritated skin.

Stop use and ask a doctor if irritation or rash develops

Keep out of reach of children. If swallowed, seek medical help or contact a Poison Control Center immediately

DOSAGE AND ADMINISTRATION

Directions: Remove cap. Turn dial to raise product. Apply evenly to underarms only. Replace cap after use.

INACTIVE INGREDIENT

Inactive Ingredients: Cetyryl Alcohol, Talc Powder, Cyclopentasiloxane, Isododecane, Stearic Acid, Isopropyl Myristate, Fragrance, Butylated Hydroxytoluene

PACKAGE LABEL

Marx for Men

Invisible Solid

Xtreme Stick

Anti-perspirant and deodorant

24 hours protection

Invisible

Net Wt/ 2oz (57g)

Distributed by Marx for Men products

Vernon, CA 90058

Made in China